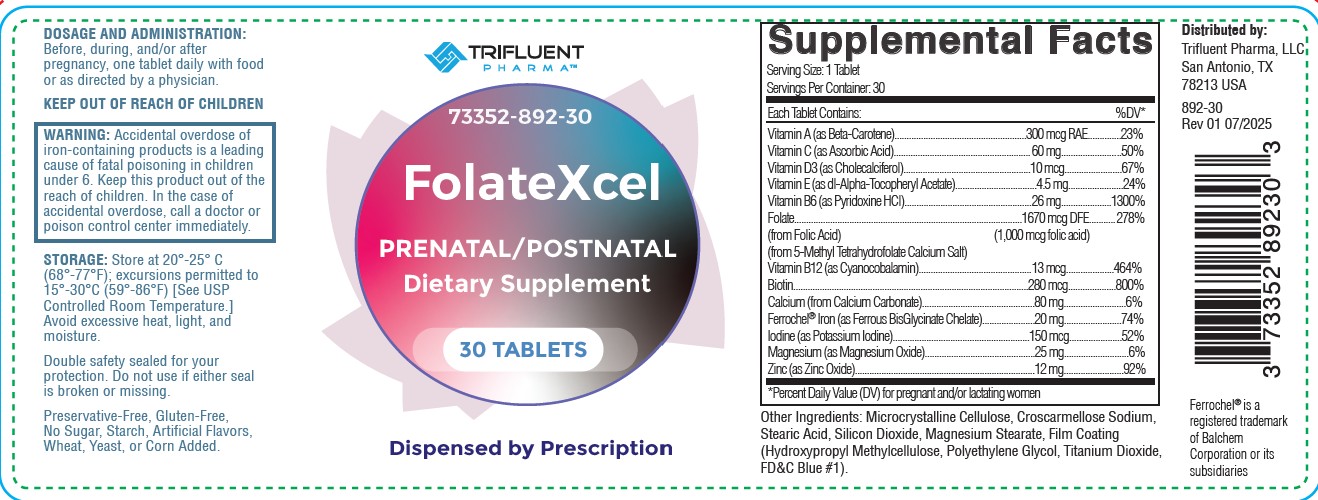 DRUG LABEL: FolateXcel
NDC: 73352-892 | Form: TABLET
Manufacturer: Trifluent Pharma
Category: other | Type: DIETARY SUPPLEMENT
Date: 20250807

ACTIVE INGREDIENTS: ASCORBIC ACID 60 mg/1 1; BETA CAROTENE 300 ug/1 1; CHOLECALCIFEROL 10 ug/1 1; .ALPHA.-TOCOPHEROL ACETATE, DL- 4.5 mg/1 1; PYRIDOXINE HCL 26 mg/1 1; FOLIC ACID 1000 ug/1 1; LEVOMEFOLATE CALCIUM 670 ug/1 1; CYANOCOBALAMIN 13 ug/1 1; BIOTIN 280 ug/1 1; CALCIUM CARBONATE 80 mg/1 1; FERROUS BISGLYCINATE 20 mg/1 1; POTASSIUM IODIDE 150 ug/1 1; MAGNESIUM OXIDE 25 mg/1 1; ZINC OXIDE 12 mg/1 1
INACTIVE INGREDIENTS: STEARIC ACID; CROSCARMELLOSE SODIUM; SILICON DIOXIDE; MAGNESIUM STEARATE; TITANIUM DIOXIDE; POLYETHYLENE GLYCOL, UNSPECIFIED; FD&C BLUE NO. 1; HYDROXYPROPYL METHYLCELLULOSE; MICROCRYSTALLINE CELLULOSE

FolateXcel
PRENATAL/POSTNATAL
Dietary Supplement

HEALTH CLAIM

FolateXcelPrenatal/Postnatal Dietary Supplement - Dispensed by Prescription

STATEMENT OF IDENTITY

FolateXcel- beta carotene, ascorbic acid, cholecalciferol, dl-alpha-tocopheryl acetate, pyridoxine hydrochloride, folic acid, 5-methyl tetrahydrofolate calcium salt, cyanocobalamin, biotin, calcium carbonate, ferrous bisglycinate chelate, potassium iodine, and magnesium oxide, zinc oxide tablet.

Serving Size: 1 Tablet; Servings Per Container: 30
Each Tablet Contains: |  | %DV
Vitamin A (as Beta-Carotene) | 300 mcg RAE | 23%
Vitamin C (as ascorbic acid) | 60 mg | 50%
Vitamin D3 (as cholecalciferol) | 10 mcg | 67%
Vitamin E (as dl-Alpha-Tocopheryl Acetate) | 4.5 mg | 24%
Vitamin B6 (as pyridoxine HCl) | 26 mg | 1300%
Folate; (From Folic Acid) (1000 mcg folic acid); (From 5-Methyl Tetrahydrofolate, Calcium Salt) | 1670 mcg DFE | 278%
Vitamin B12 (as Cyanocobalamine) | 13 mcg | 464%
Biotin | 280 mcg | 800%
Calcium (from Calcium Carbonate) | 80 mg | 6%
FerrochelTM Iron (as ferrous BisGlycinate Chelate) | 20 mg | 74%
Iodine (as potassium iodide) | 150 mcg | 52%
Magnesium (as Magnesium oxide) | 25 mg | 6%
Zinc (as Zinc Oxide) 12 mg 92%

*Percent Daily Value (DV) for pregnant and/or lactating women

OTHER INGREDIENTS: Modified Cellulose, Croscarmellose Sodium, Stearic Acid, Silicon Dioxide, Magnesium Stearate. Film Coating: (Hydroxypropyl Methylcellulose, Polyethylene Glycol, Titanium Dioxide, FD&C Blue#1).

DESCRIPTION

Preservative-Free, Gluten-Free, No Sugar, Starch, Artificial Flavors, Wheat, Yeast, or Corn Added.

Double safety cealed for your portection. Do not sue if either seal is broken or missing.

DOSAGE AND ADMINISTRATION

Before, during and/or after pregnancy, one tablet daily with food or as directed by a physician.

STORAGE

Store at 20°-25°C (68°-77°F) excursions permitted to 15°-30°C (59°-86°F) [See USP Controlled Room Temperature.] Avoid excessive heat, light
and moisture.

Distributed by:

Trifluent Pharma, LLC.

San Antonio, TX

892039

Rev 01 07/2025

Ferrochel is a registered trademark of Balchem Corporation or its subsidiares.

WARNING

Accidental overdose of iron-containing products is a leading cause of fatal poisoning in Children under 6. Keep this product out of the reach of children. In the case of acceidental overdose, call a docotr or poison control center immediately.

KEEP OUT OF REACH OF CHILDREN